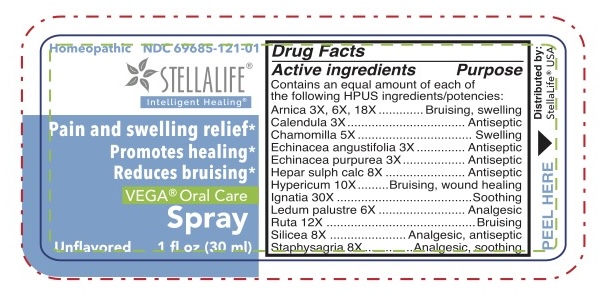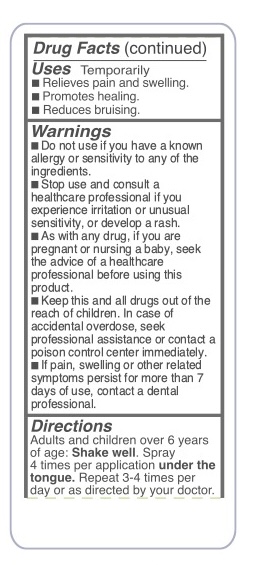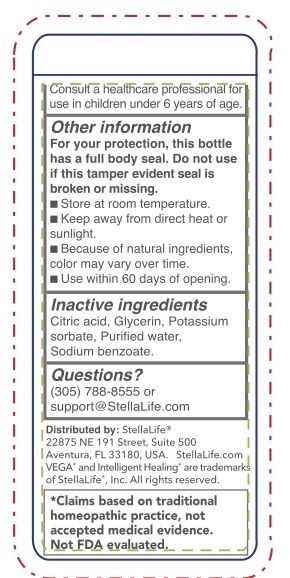 DRUG LABEL: StellaLife VEGA Oral Care
NDC: 69685-121 | Form: SPRAY
Manufacturer: StellaLife, Inc.
Category: homeopathic | Type: HUMAN OTC DRUG LABEL
Date: 20251222

ACTIVE INGREDIENTS: HYPERICUM PERFORATUM 10 [hp_X]/1 mL; STRYCHNOS IGNATII SEED 30 [hp_X]/1 mL; SILICON DIOXIDE 8 [hp_X]/1 mL; CALENDULA OFFICINALIS FLOWERING TOP 3 [hp_X]/1 mL; ECHINACEA ANGUSTIFOLIA 3 [hp_X]/1 mL; CALCIUM SULFIDE 8 [hp_X]/1 mL; RUTA GRAVEOLENS FLOWERING TOP 12 [hp_X]/1 mL; ARNICA MONTANA 3 [hp_X]/1 mL; MATRICARIA RECUTITA 5 [hp_X]/1 mL; ECHINACEA PURPUREA 3 [hp_X]/1 mL; LEDUM PALUSTRE TWIG 6 [hp_X]/1 mL; DELPHINIUM STAPHISAGRIA SEED 8 [hp_X]/1 mL
INACTIVE INGREDIENTS: SODIUM BENZOATE; CITRIC ACID MONOHYDRATE; GLYCERIN; POTASSIUM SORBATE; WATER

SPRAY - Unflavored - StellaLife

Active Ingredients

Arnica 3X, 6X, 18X, Calendula 3X, Chamomilla 5X, Echinacea angustifolia 3X, Echinacea purpurea 3X, Hepar sulph calc 8X, Hypericum 10X, lgnatia 30X, Ruta 12X, Silicea 8X, Staphysagria 8X

Purpose

Active Ingredient | Purpose
Arnica | Bruising, swelling
Calendula | Antiseptic
Chamomilla | Swelling
Echinacea angustifolia | Antiseptic
Echinacea purpurea | Antiseptic
Hepar sulph calc | Antiseptic
Hypericum | Bruising, wound healing
lgnatia | Soothing
Ledum palustre | Analgesic
Ruta | Bruising
Silicea | Analgesic, antiseptic
Staphysagria | Analgesic, soothing

Keep out of reach of children

■ Keep this and all drugs out of the reach of children. In case of accidental overdose, seek professional assistance or contact a poison control center immediately.

Pregnancy

■ As with any drug, if you are pregnant or nursing a baby, seek the advice of a healthcare professional before using this product.

Warnings

For your protection, this bottle has a full body seal. Do not use if this tamper evident seal is broken or missing.

Directions

Adults and children over 6 years of age: Shake well. Spray 3-4 times per application under the tongue. Repeat 3-4 times per day or as directed by your doctor. Consult a healthcare professional for use in children under 6 years of age.

Uses

■ Relieves pain and swelling.

■ Promotes healing.

■ Reducing bruising.

■ Do not use if you have a known allergy or sensitivity to any of the ingredients.

Stop use

■ Stop use and consult a healthcare professional if you experience irritation or unusual sensitivity, or develop a rash.

Ask dental professional

■ If pain, swelling or other related symptoms persist for more than 7 days of use, contact a dental professional.

Other information

■ Store at room temperature.

■ Keep away from direct heat or sunlight.

■ Because of natural ingredients. color may vary overtime.

■ Use within 60 days of opening

Questions?

(305) 788-8555 or

Support@StellaLife.com

Inactive Ingredients

Citric acid, Glycerine, Potassium sorbate, Purified water, Sodium Benzoate